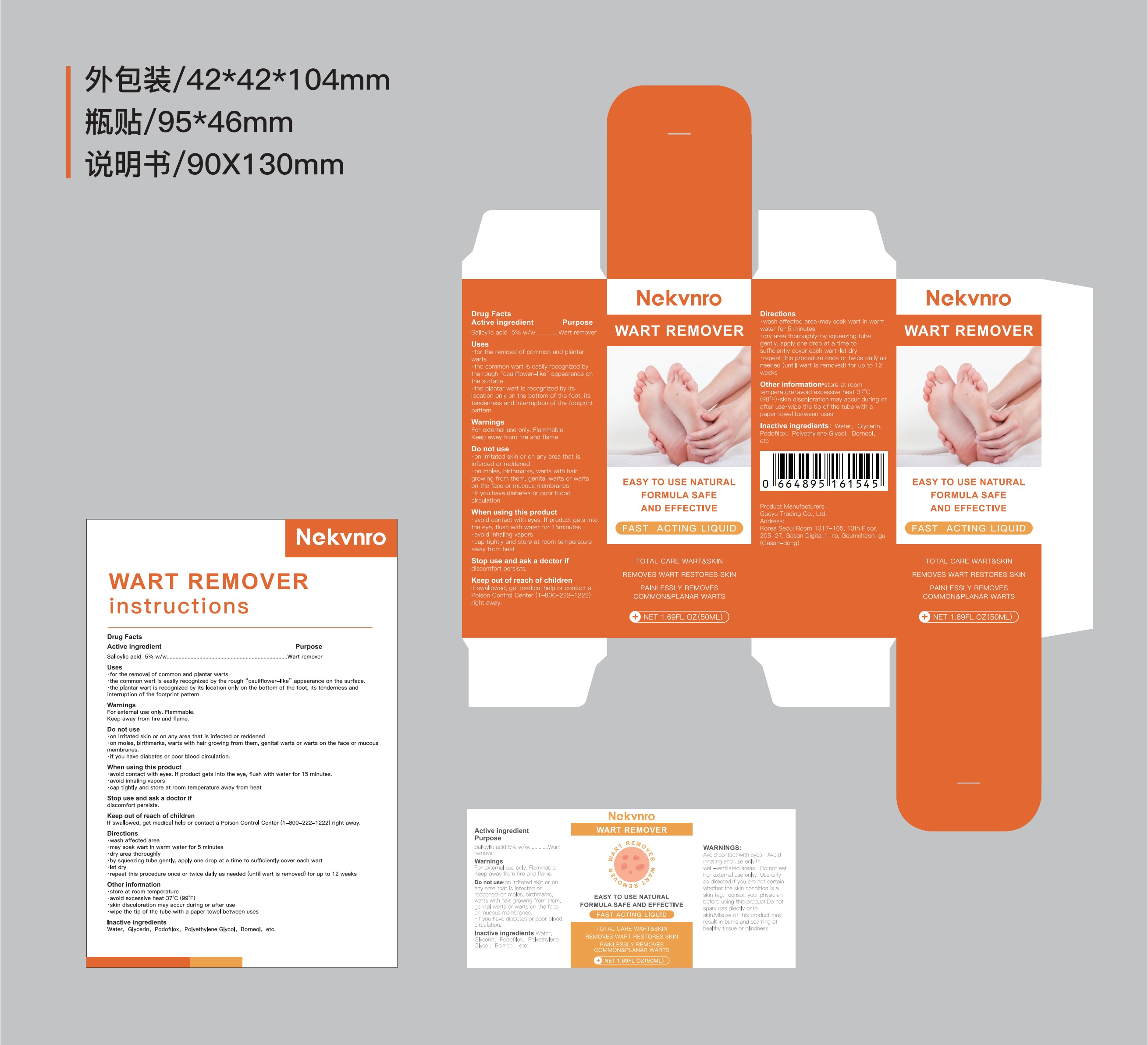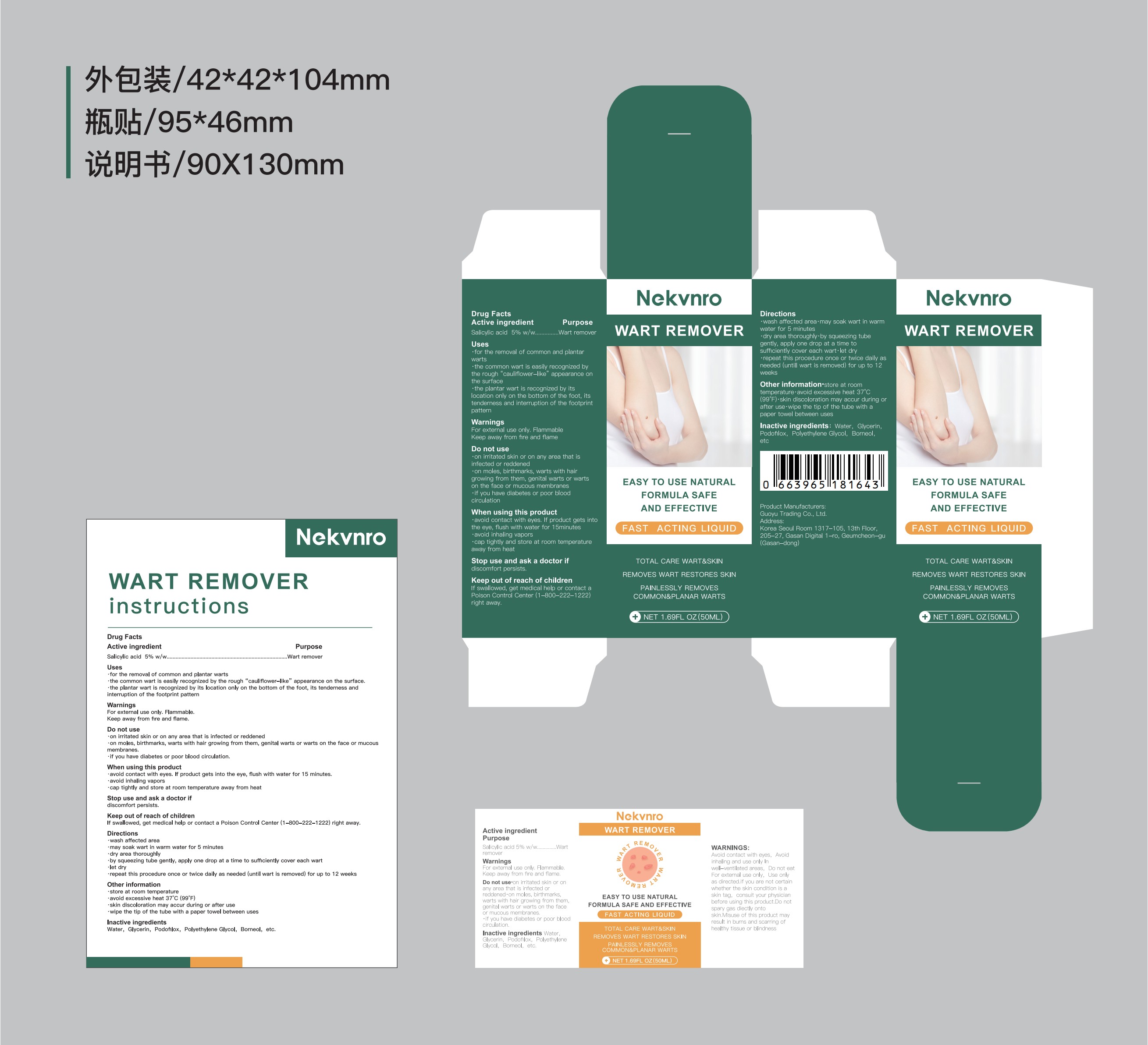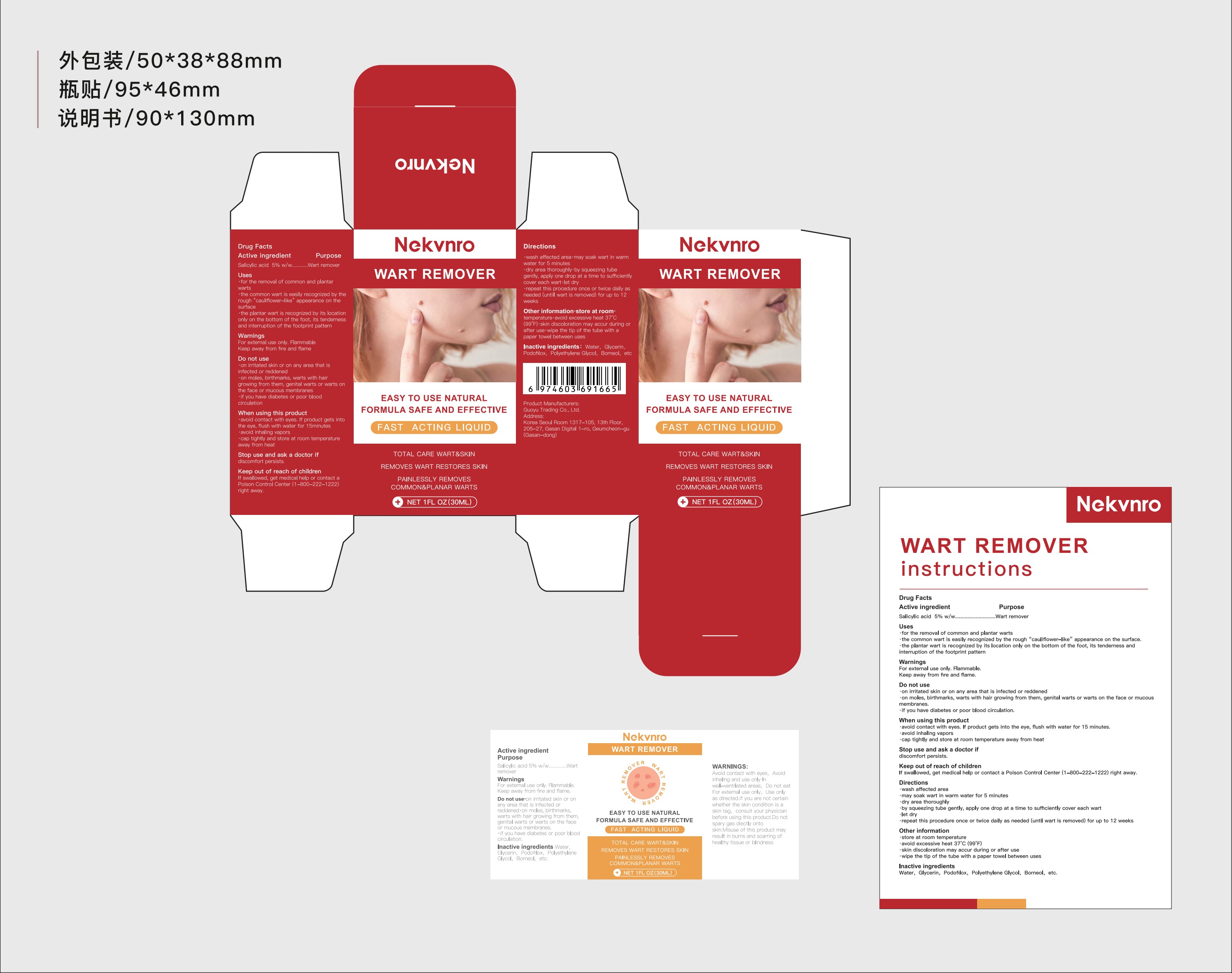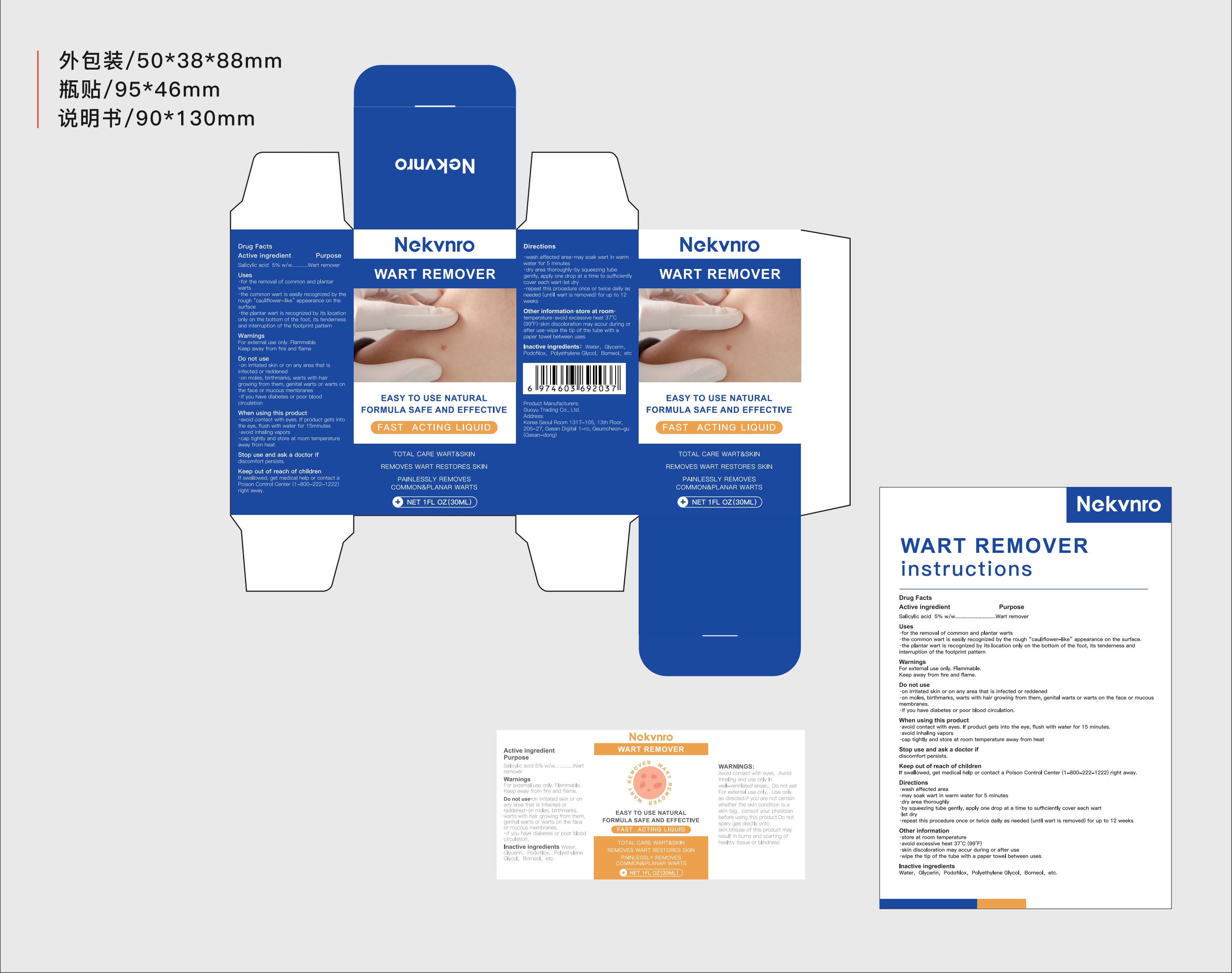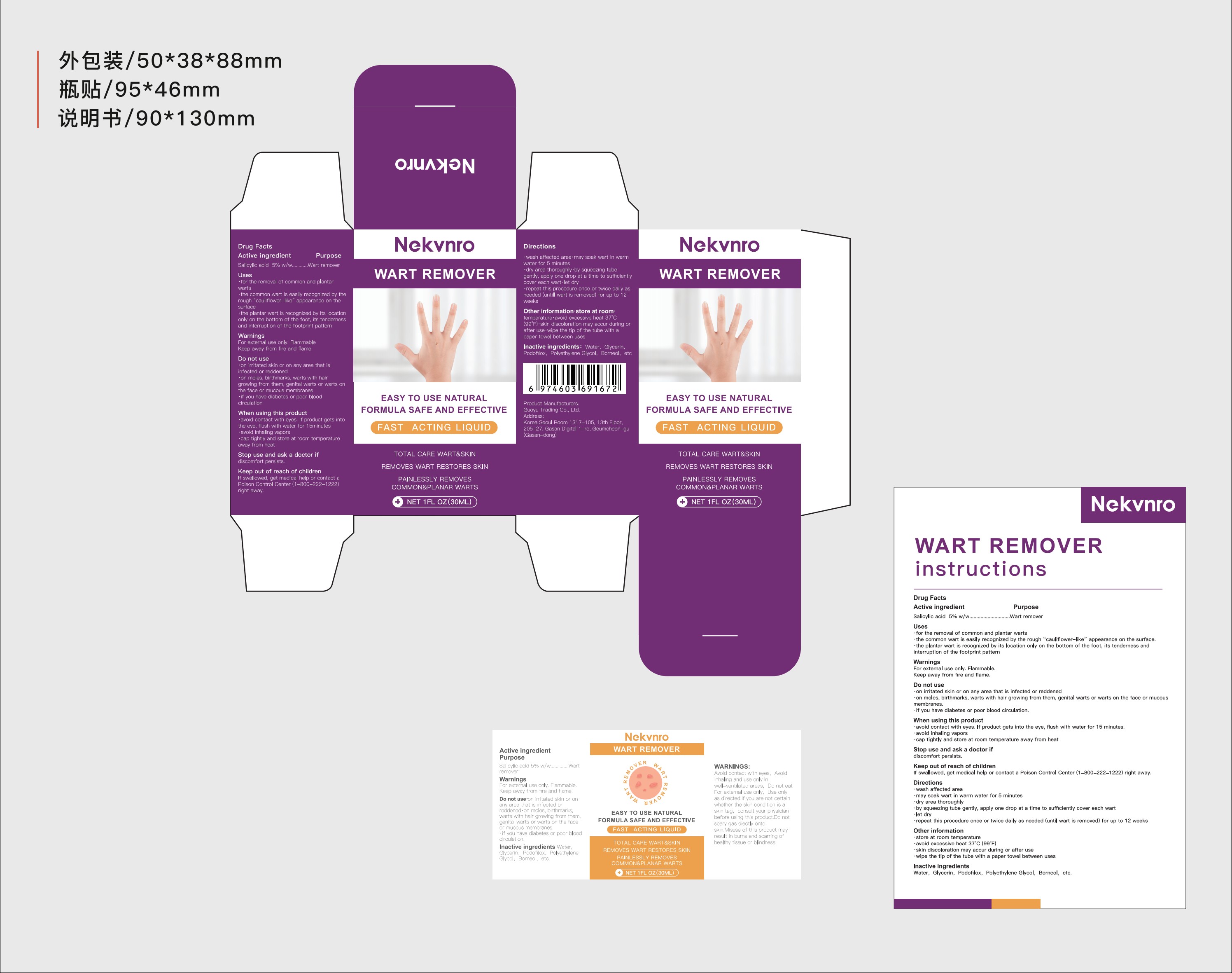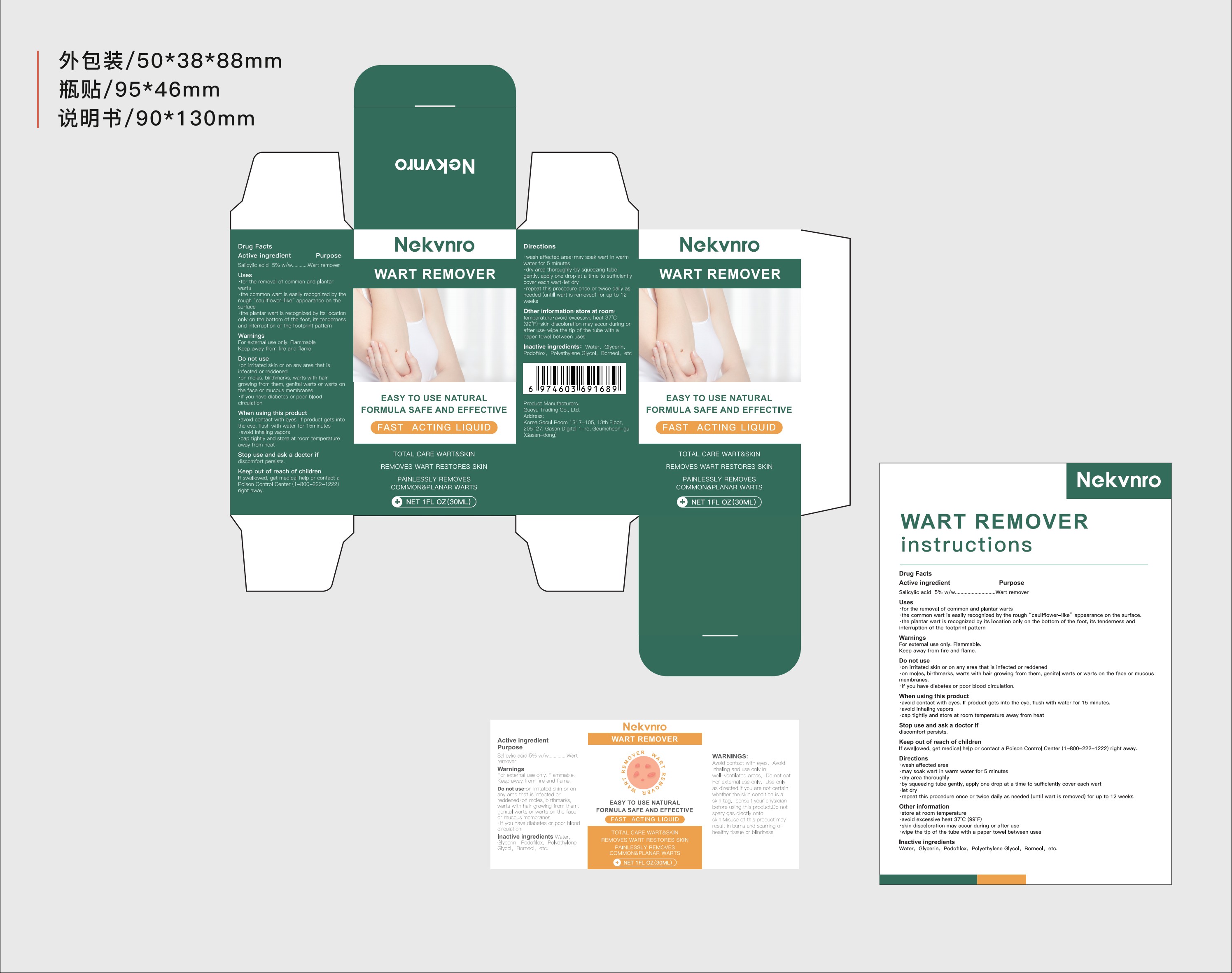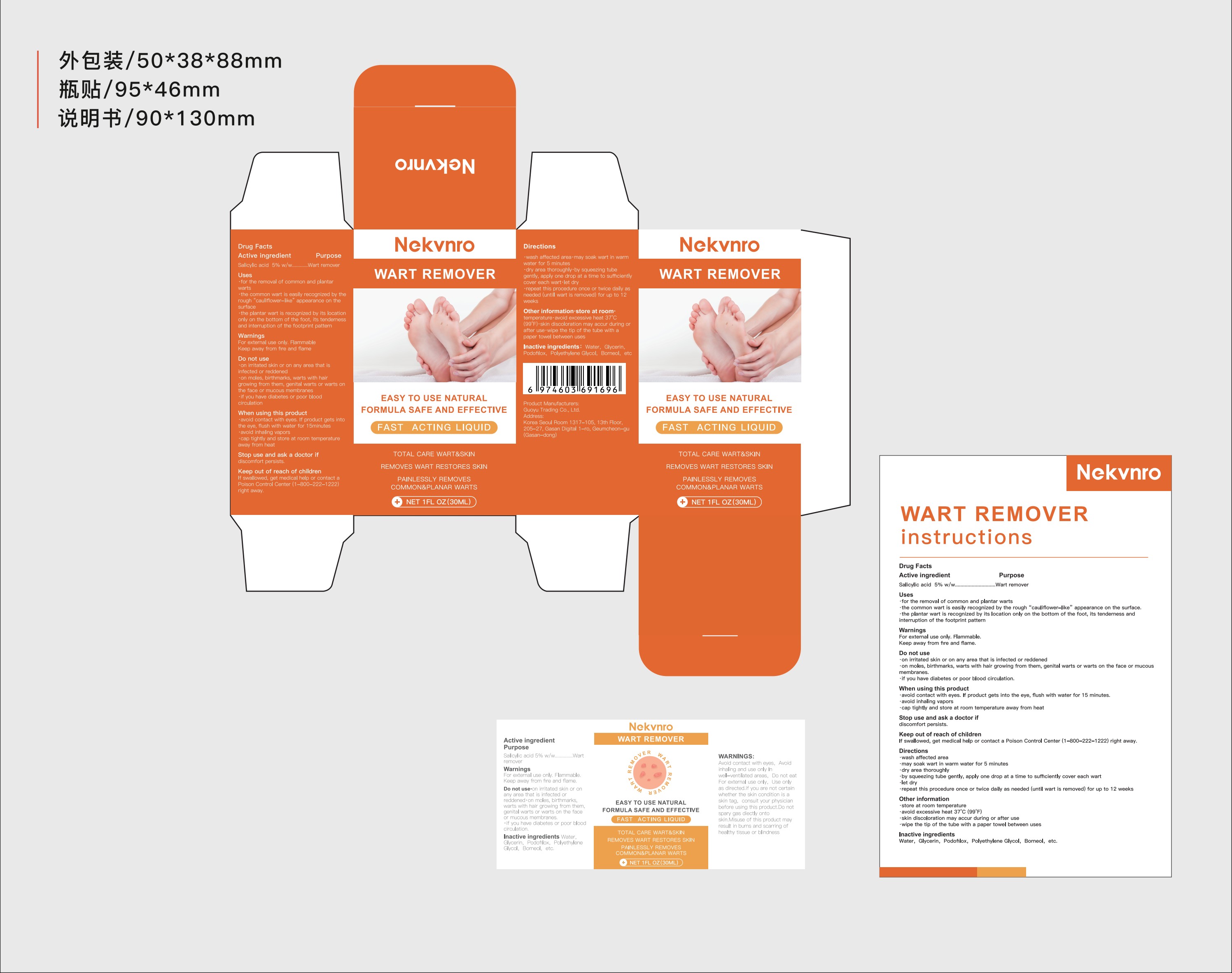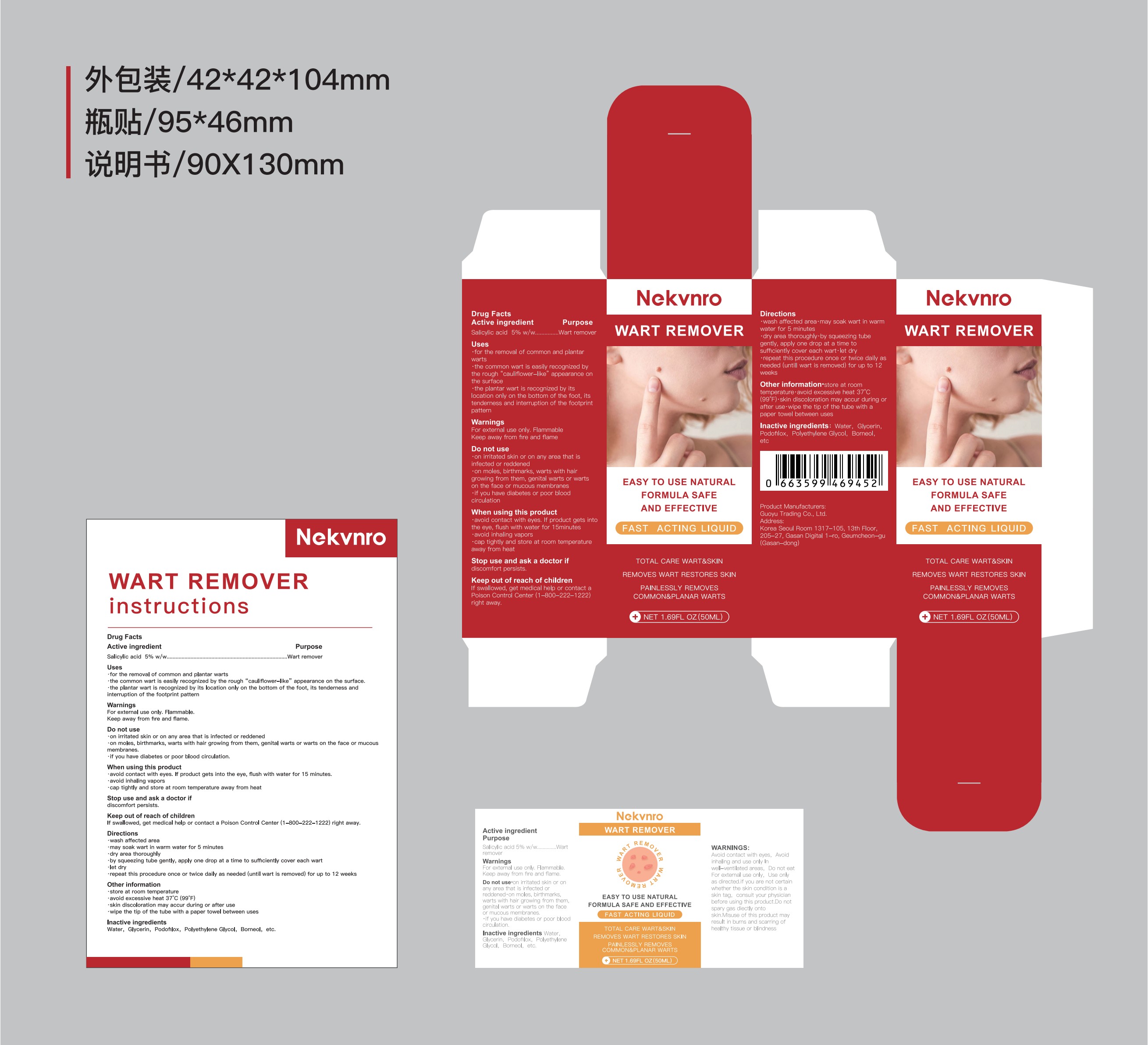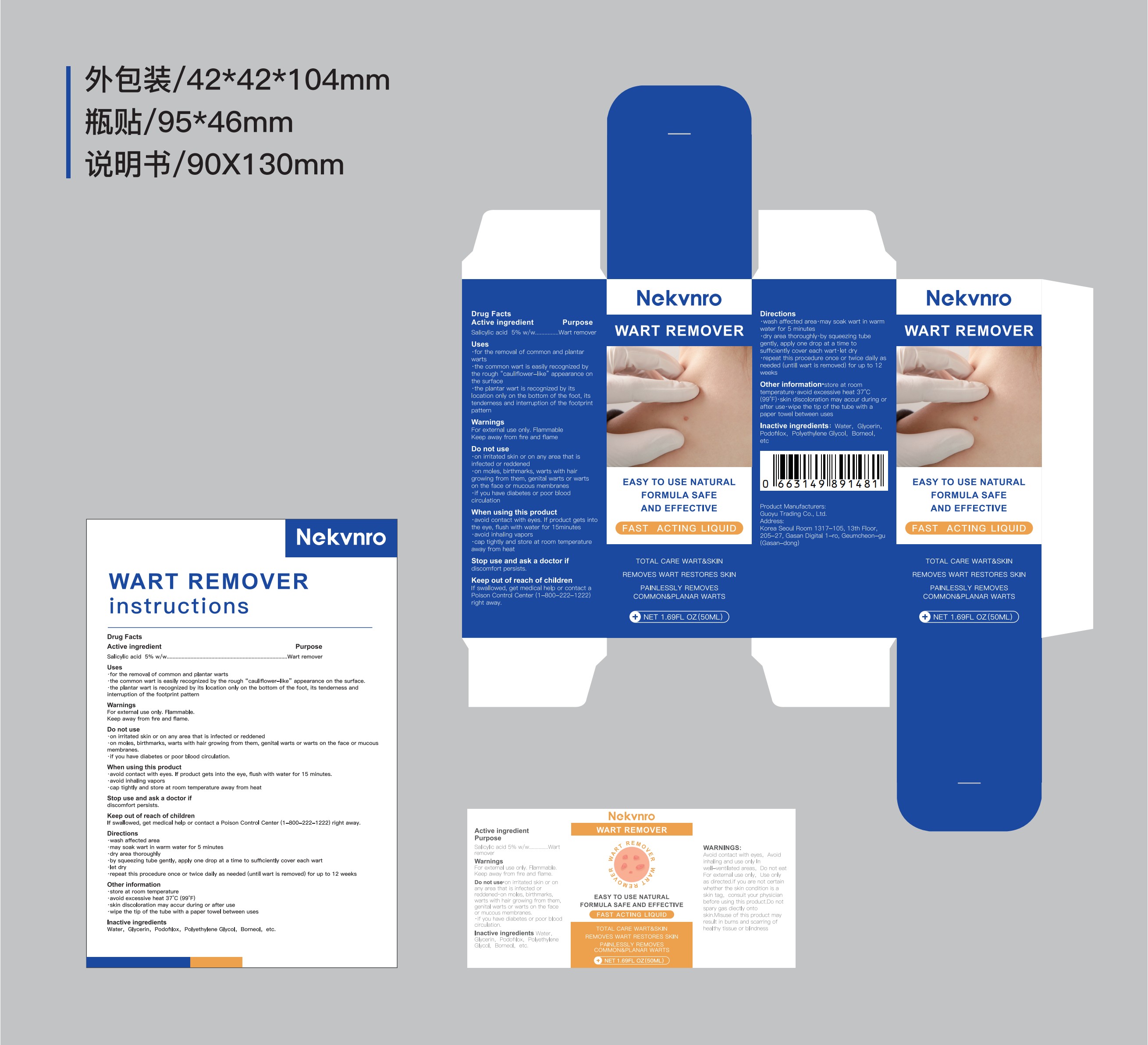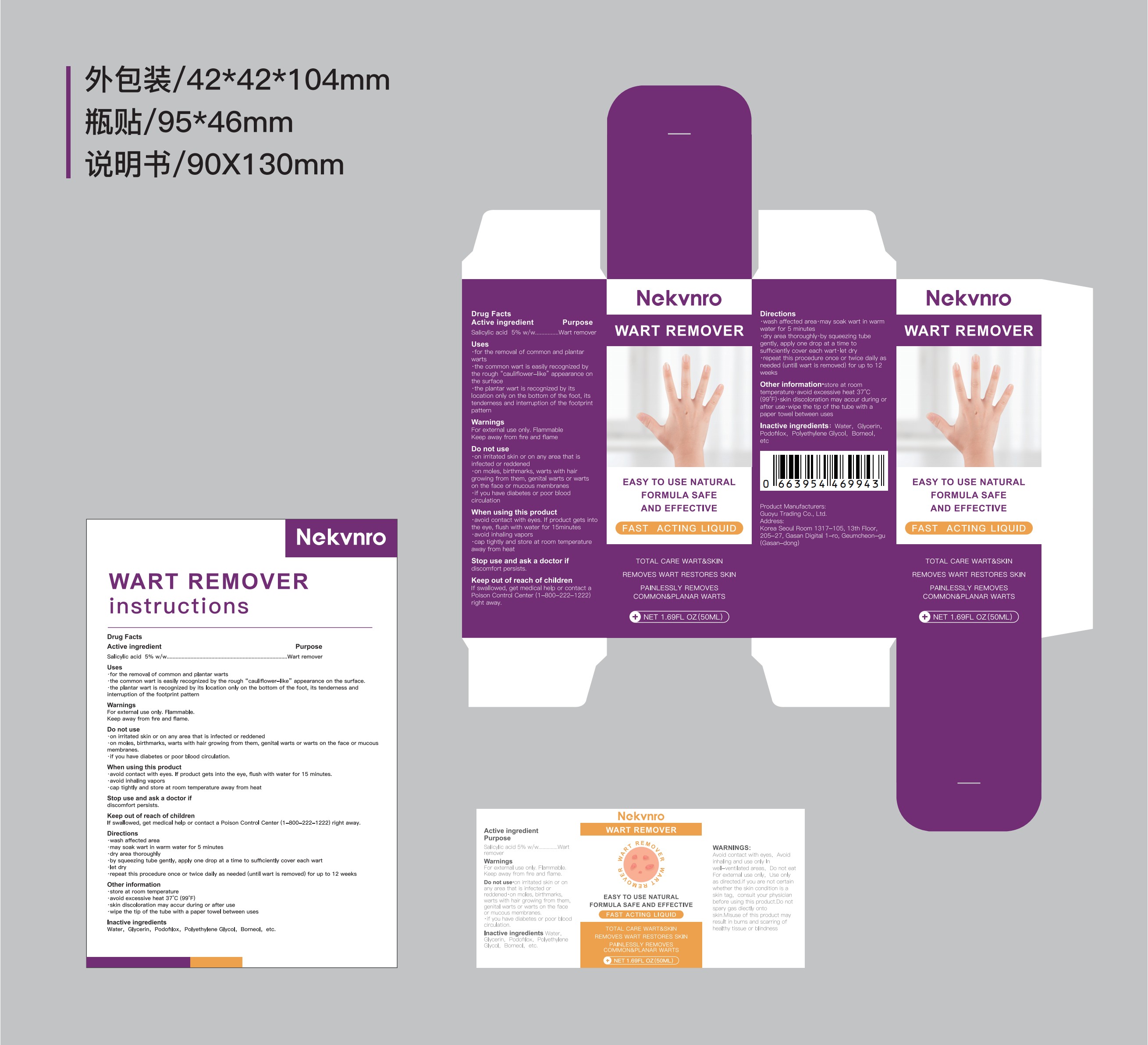 DRUG LABEL: Nekvnro Wart Remover
NDC: 84844-013 | Form: LIQUID
Manufacturer: Guoyu Trading Co., Ltd.
Category: otc | Type: HUMAN OTC DRUG LABEL
Date: 20241106

ACTIVE INGREDIENTS: SALICYLIC ACID 5 g/100 mL
INACTIVE INGREDIENTS: WATER; GLYCERIN; POLYETHYLENE GLYCOL, UNSPECIFIED; BORNEOL; PODOFILOX

84844-013

Active Ingredient

Salicylic acid 5%

Purpose

Wart remover

Use

·for the removal of common and plantar warts
·the common wart is easily recognized by the rough “cauliflower-like” appearance on the surface.
·the plantar wart is recognized by its location only on the bottom of the foot, its tenderness and interruption of the footprint pattern

Warnings

For external use only. Flammable.
Keep away from fire and flame.

Do not use

·on irritated skin or on any area that is infected or reddened
·on moles, birthmarks, warts with hair growing from them, genital warts or warts on the face or mucous membranes.
·if you have diabetes or poor blood circulation.

When Using

·avoid contact with eyes. If product gets into the eye, flush with water for 15 minutes.
·avoid inhaling vapors
·cap tightly and store at room temperature away from heat

Stop Use

and ask a doctor if
discomfort persists.

Ask Doctor

discomfort persists.

Keep Oot Of Reach Of Children

If swallowed, get medical help or contact a Poison Control Center (1-800-222-1222) right away.

Directions

·wash affected area
·may soak wart in warm water for 5 minutes
·dry area thoroughly
·by squeezing tube gently, apply one drop at a time to sufficiently cover each wart
·let dry
·repeat this procedure once or twice daily as needed (until wart is removed) for up to 12 weeks

Other information

·store at room temperature
·avoid excessive heat 37°C (99°F)
·skin discoloration may accur during or after use
·wipe the tip of the tube with a paper towel between uses

Inactive ingredients

Water，Glycerin，Podofilox，Polyethylene Glycol，Borneol，etc.